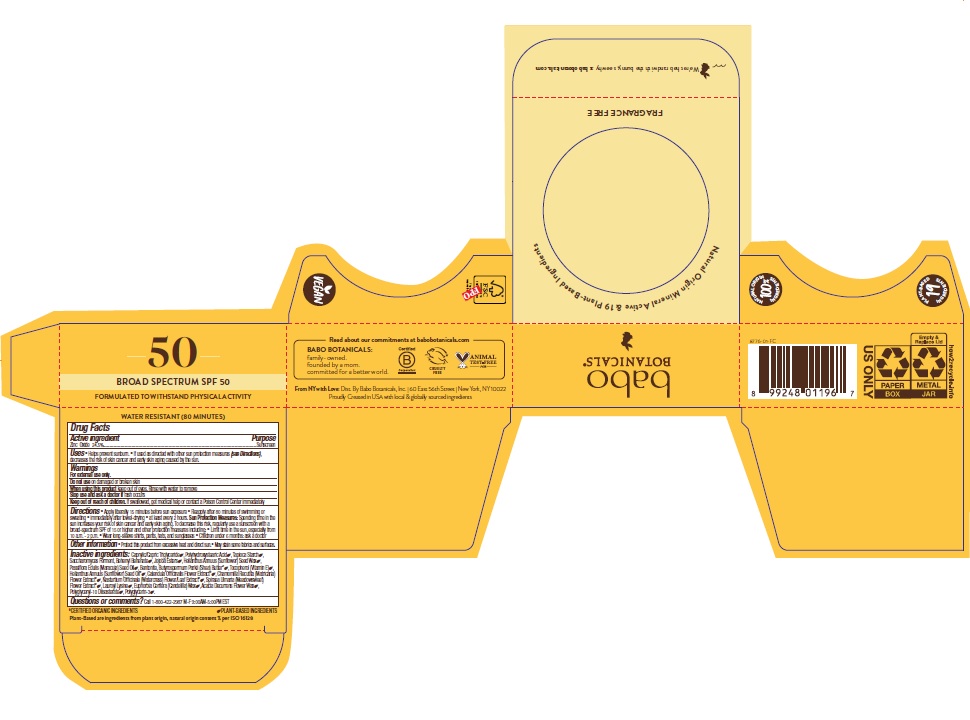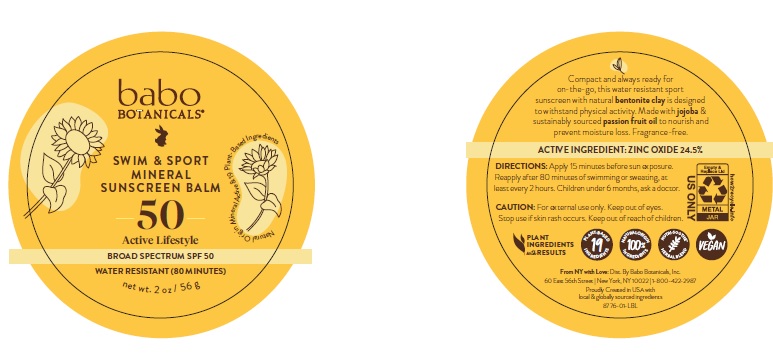 DRUG LABEL: Babo Botanicals Swim and Sport Mineral Sunscreen Balm SPF 50
NDC: 79265-8776 | Form: SALVE
Manufacturer: Babo Botanicals, Inc.
Category: otc | Type: HUMAN OTC DRUG LABEL
Date: 20241212

ACTIVE INGREDIENTS: ZINC OXIDE 245 mg/1 g
INACTIVE INGREDIENTS: POLYHYDROXYSTEARIC ACID (2300 MW); BENTONITE; SHEA BUTTER; LAUROYL LYSINE; FILIPENDULA ULMARIA FLOWER; PASSIFLORA EDULIS SEED OIL; ACACIA DECURRENS FLOWER WAX; BEHENYL BEHENATE; CANDELILLA WAX; SUNFLOWER OIL; POLYGLYCERIN-3; MEDIUM-CHAIN TRIGLYCERIDES; JOJOBA OIL, RANDOMIZED; TOCOPHEROL; HELIANTHUS ANNUUS SEED WAX; CALENDULA OFFICINALIS FLOWER; CHAMOMILE; NASTURTIUM OFFICINALE; STARCH, TAPIOCA

Babo Botanicals Swim and Sport Mineral Sunscreen Balm SPF 50

Active ingredient

Zinc Oxide 24.5%

Purpose

Sunscreen

Uses

- Helps prevent sunburn.
- If used as directed with other sun protection measures (see Directions), decreases the risk of skin cancer and early skin aging caused by the sun.

Warnings

For external use only.

Do not use

on damaged or broken skin.

When using this product

- keep out of eyes. Rinse with water to remove.

Stop use and ask doctor

- if rash occurs.

Keep out of reach of children.

If swallowed, get medical help or contact a Poison Control Center immediately.

Directions

- Apply liberally 15 minutes before sun exposure.
- Reapply after 80 minutes of swimming or sweating, immediately after towel-drying, at least every two hours.

Sun Protection Measures Spending time in the sun increases your risk of skin cancer and early skin aging. To decrease this risk, regularly use a sunscreen with a Broad Spectrum SPF of 15 or higher and other sun protection measures including:

- Limit time in the sun, especially from 10 a.m. - 2 p.m.
- Wear long-sleeve shirts, pants, hats and sunglasses.
- Children under 6 months of age: ask a doctor

Other information

- Protect this product from excessive heat and direct sun.
- May stain some fabrics and surfaces.

Inactive ingredients

Caprylic/Capric Triglyceride, Polyhydroxystearic Acid, Tapioca Starch, Saccharomyces Ferment, Behenyl Behenate, Jojoba Esters, Helianthus Annuus (Sunflower) Seed Wax, Passiflora Edulis (Maracuja) Seed Oil, Bentonite, Butyrospermum Parkii (Shea) Butter, Tocopherol (Vitamin E), Helianthus Annuus (Sunflower) Seed Oil, Calendula Officinalis Flower Extract, Chamomilla Recutita (Matricaria) Flower Extract, Nasturtium Officinale (Watercress) Flower/Leaf Extract, Spiraea Ulmaria (Meadowsweet) Flower Extract, Lauroyl Lysine, Euphorbia Cerifera (Candelilla) Wax, Acacia Decurrens Flower Wax, Polyglyceryl-10 Diisosterate, Polyglycerin-3.

Questions or comments?

Call 1-800-422-2987 M-F

9:00am - 5:00pm EST